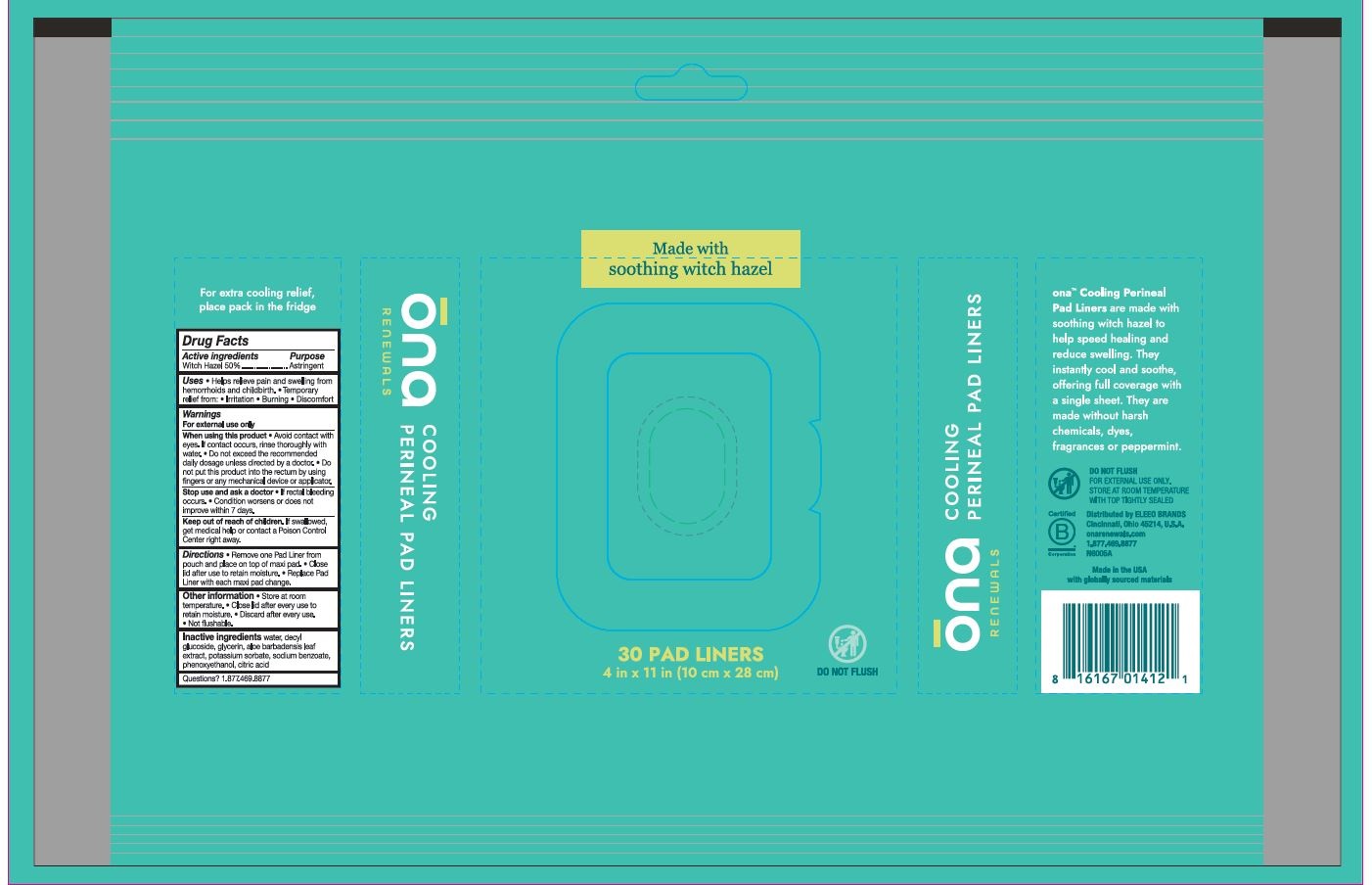 DRUG LABEL: Cooling Perineal Pad Liners
NDC: 79747-010 | Form: CLOTH
Manufacturer: ELEEO BRANDS LLC
Category: otc | Type: HUMAN OTC DRUG LABEL
Date: 20250825

ACTIVE INGREDIENTS: WITCH HAZEL 0.5 mg/1 mL
INACTIVE INGREDIENTS: DECYL GLUCOSIDE; SODIUM BENZOATE; POTASSIUM SORBATE; WATER; PHENOXYETHANOL; ALOE BARBADENSIS LEAF; CITRIC ACID; GLYCERIN

ACTIVE INGREDIENT

Witch Hazel 50%

PURPOSE

* Help relieve pain and swelling from hemorrhoids and childbirth

* Temporary relief from: irritation, burning, discomfort

INDICATIONS AND USAGE

* Help relieve pain and swelling from hemorrhoids and childbirth

* Temporary relief from: irritation, burning, discomfort

WARNINGS

For external use only

When using this product:

* Avoid contact with eyes. If contact occurs, rinse thorougly with water.

* Do not exceed the recommended daily dosage unless directed by doctor.

* Do not put this product into the rectum by using fingers or any mechanical device or applicator.

Stop use and ask and ask a dotor if

* Rectal bleeding occurs.

* Condition worsens or does not improve within 7 days.

KEEP OUT OF REACH OF CHILDREN

If swallowed, get medical help or contact a Poison Control Center right away.

DOSAGE AND ADMINISTRATION

* Remove one liner from the pack and reseal the lid.

* Place the liner on top of a maxi pad.

* Close lid after use to retain moisture.

* Replace Pad liner with each maxi pad change

INACTIVE INGREDIENT

Water, aloe barbadensis leaf extract,, citric acid, decyl glucoside, glycerin, potassium sorbate, sodium benzoate, phenoxyethanol

STORAGE AND HANDLING

* Store at room temperature

* Single use per wipe

* Close lid after every use to retain moisture

* Discard after every use

* Not flushable